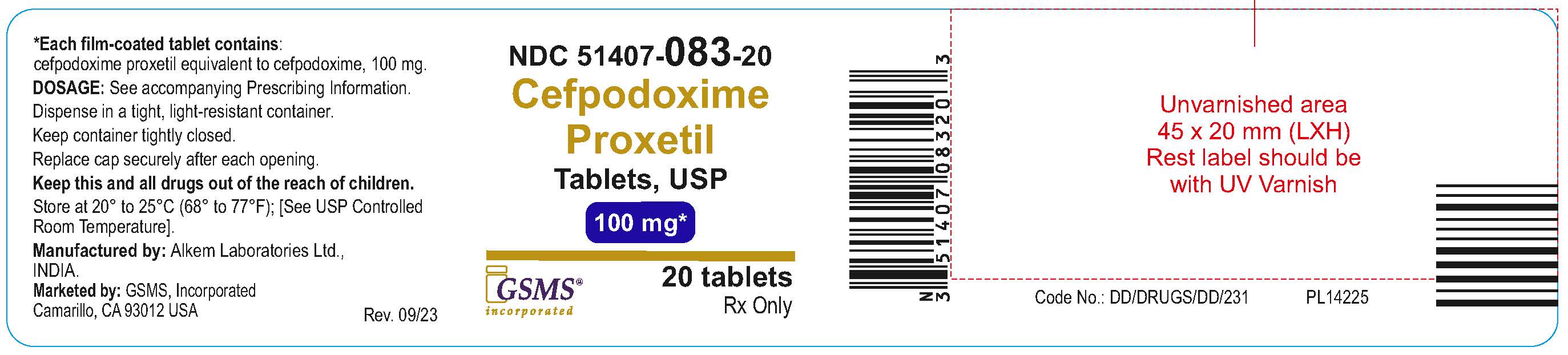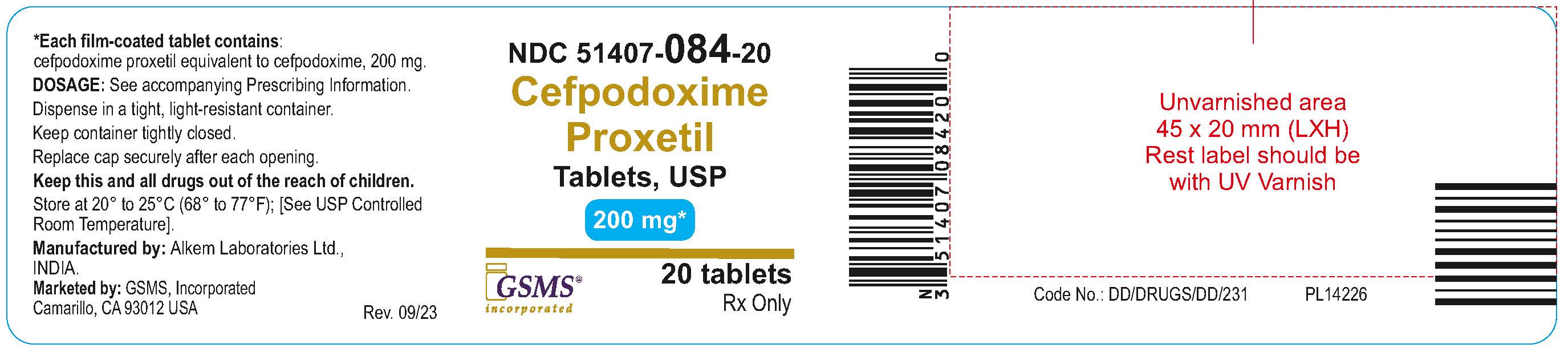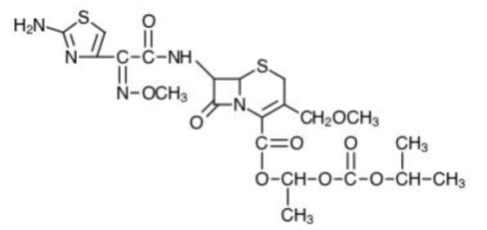 DRUG LABEL: Cefpodoxime Proxetil
NDC: 51407-084 | Form: TABLET, FILM COATED
Manufacturer: Golden State Medical Supply, Inc.
Category: prescription | Type: HUMAN PRESCRIPTION DRUG LABEL
Date: 20250218

ACTIVE INGREDIENTS: CEFPODOXIME PROXETIL 200 mg/1 1
INACTIVE INGREDIENTS: SILICON DIOXIDE; CROSPOVIDONE, UNSPECIFIED; FD&C YELLOW NO. 6; HYDROXYPROPYL CELLULOSE, UNSPECIFIED; HYPROMELLOSES; FERRIC OXIDE RED; LACTOSE MONOHYDRATE; POLYETHYLENE GLYCOL, UNSPECIFIED; MAGNESIUM STEARATE; SODIUM LAURYL SULFATE; TITANIUM DIOXIDE; CARBOXYMETHYLCELLULOSE CALCIUM

Cefpodoxime Proxetil Tablets.

Cefpodoxime Proxetil Tablets, USP

Rx only
To reduce the development of drug-resistant bacteria and maintain the effectiveness of cefpodoxime proxetil tablets, USP and other antibacterial drugs, cefpodoxime proxetil tablets, USP should be used only to treat or prevent infections that are proven or strongly suspected to be caused by bacteria.
For Oral Use Only

DESCRIPTION

Cefpodoxime proxetil is an orally administered, extended spectrum, semi-synthetic antibiotic of the cephalosporin class. The chemical name is (RS)-1(isopropoxycarbonyloxy) ethyl (+)-(6R, 7R)-7-[2-(2-amino-4-thiazolyl)-2-{(Z) methoxyimino} acetamido]-3-methoxymethyl-8-oxo-5-thia-1-azabicyclo [4.2.0]oct-2-ene-2-carboxylate.

Its empirical formula is C21H27N5O9S2 and its structural formula is represented below:

The molecular weight of cefpodoxime proxetil is 557.6.
Cefpodoxime proxetil is a prodrug; its active metabolite is cefpodoxime. All doses of cefpodoxime proxetil in this insert are expressed in terms of the active cefpodoxime moiety. The drug is supplied as film-coated tablets.
Cefpodoxime proxetil tablets, USP contain cefpodoxime proxetil USP equivalent to 100 mg or 200 mg of cefpodoxime activity. Each film-coated tablet contains the following inactive ingredients:
Carboxymethyl cellulose calcium, colloidal silicon dioxide, crospovidone, FD&C Yellow No. 6, hydroxypropyl cellulose, hypromellose, iron oxide red, lactose monohydrate, macrogol, magnesium stearate, sodium lauryl sulfate and titanium dioxide.

CLINICAL PHARMACOLOGY

Absorption and Excretion
Cefpodoxime proxetil is a prodrug that is absorbed from the gastrointestinal tract and de-esterified to its active metabolite, cefpodoxime. Following oral administration of 100 mg of cefpodoxime proxetil to fasting subjects, approximately 50% of the administered cefpodoxime dose was absorbed systemically. Over the recommended dosing range (100 to 400 mg), approximately 29 to 33% of the administered cefpodoxime dose was excreted unchanged in the urine in 12 hours. There is minimal metabolism of cefpodoxime in vivo.
Effects of Food
The extent of absorption (mean AUC) and the mean peak plasma concentration increased when film coated tablets were administered with food. Following a 200 mg tablet dose taken with food, the AUC was 21 to 33% higher than under fasting conditions, and the peak plasma concentration averaged 3.1 mcg/mL in fed subjects versus 2.6 mcg/mL in fasted subjects. Time to peak concentration was not significantly different between fed and fasted subjects.
When a 200 mg dose of the suspension was taken with food, the extent of absorption (mean AUC) and mean peak plasma concentration in fed subjects were not significantly different from fasted subjects, but the rate of absorption was slower with food (48% increase in Tmax).
Pharmacokinetics of cefpodoxime proxetil film-coated tablets
Over the recommended dosing range (100 to 400 mg), the rate and extent of cefpodoxime absorption exhibited dose-dependency; dose-normalized Cmax and AUC decreased by up to 32% with increasing dose. Over the recommended dosing range, the Tmax was approximately 2 to 3 hours and the T1/2 ranged from 2.09 to 2.84 hours. Mean Cmax was 1.4 mcg/mL for the 100 mg dose, 2.3 mcg/mL for the 200 mg dose, and 3.9 mcg/mL for the 400 mg dose. In patients with normal renal function, neither accumulation nor significant changes in other pharmacokinetic parameters were noted following multiple oral doses of up to 400 mg Q 12 hours.
Cefpodoxime Plasma Levels (mcg/mL) in Fasted Adults After Film-coated Tablet Administration (Single Dose)

Dose | Time after Oral Ingestion
(Cefpodoxime Equivalents) | 1hr | 2hr | 3hr | 4hr | 6hr | 8hr | 12hr
100 mg | 0.98 | 1.4 | 1.3 | 1 | 0.59 | 0.29 | 0.08
200 mg | 1.5 | 2.2 | 2.2 | 1.8 | 1.2 | 0.62 | 0.18
400 mg | 2.2 | 3.7 | 3.8 | 3.3 | 2.3 | 1.3 | 0.38

Distribution
Protein binding of cefpodoxime ranges from 22 to 33% in serum and from 21 to 29% in plasma.
Skin Blister
Following multiple-dose administration every 12 hours for 5 days of 200 mg or 400 mg cefpodoxime proxetil, the mean maximum cefpodoxime concentration in skin blister fluid averaged 1.6 and 2.8 mcg/mL, respectively. Skin blister fluid cefpodoxime levels at 12 hours after dosing averaged 0.2 and 0.4 mcg/mL for the 200 mg and 400 mg multiple-dose regimens, respectively.
Tonsil Tissue
Following a single, oral 100 mg cefpodoxime proxetil film-coated tablet, the mean maximum cefpodoxime concentration in tonsil tissue averaged 0.24 mcg/g at 4 hours post-dosing and 0.09 mcg/g at 7 hours post-dosing. Equilibrium was achieved between plasma and tonsil tissue within 4 hours of dosing. No detection of cefpodoxime in tonsillar tissue was reported 12 hours after dosing. These results demonstrated that concentrations of cefpodoxime exceeded the MIC90 of S. pyogenes for at least 7 hours after dosing of 100 mg of cefpodoxime proxetil.
Lung Tissue
Following a single, oral 200 mg cefpodoxime proxetil film-coated tablet, the mean maximum cefpodoxime concentration in lung tissue averaged 0.63 mcg/g at 3 hours post-dosing, 0.52 mcg/g at 6 hours postdosing, and 0.19 mcg/g at 12 hours post-dosing. The results of this study indicated that cefpodoxime penetrated into lung tissue and produced sustained drug concentrations for at least 12 hours after dosing at levels that exceeded the MIC90 for S. pneumoniae and H. influenzae.
CSF
Adequate data on CSF levels of cefpodoxime are not available.
Effects of Decreased Renal Function
Elimination of cefpodoxime is reduced in patients with moderate to severe renal impairment (<50 mL/min creatinine clearance). (See PRECAUTIONS and DOSAGE AND ADMINISTRATION.) In subjects with mild impairment of renal function (50 to 80 mL/min creatinine clearance), the average plasma half-life of cefpodoxime was 3.5 hours. In subjects with moderate (30 to 49 mL/min creatinine clearance) or severe renal impairment (5 to 29 mL/min creatinine clearance), the half-life increased to 5.9 and 9.8 hours, respectively. Approximately 23% of the administered dose was cleared from the body during a standard 3-hour hemodialysis procedure.
Effect of Hepatic Impairment (cirrhosis)
Absorption was somewhat diminished and elimination unchanged in patients with cirrhosis. The mean cefpodoxime T1/2 and renal clearance in cirrhotic patients were similar to those derived in studies of healthy subjects. Ascites did not appear to affect values in cirrhotic subjects. No dosage adjustment is recommended in this patient population.
Pharmacokinetics in Elderly Subjects
Elderly subjects do not require dosage adjustments unless they have diminished renal function. (See PRECAUTIONS.) In healthy geriatric subjects, cefpodoxime half-life in plasma averaged 4.2 hours (vs 3.3 in younger subjects) and urinary recovery averaged 21% after a 400 mg dose was administered every 12 hours. Other pharmacokinetic parameters (Cmax, AUC, and Tmax) were unchanged relative to those observed in healthy young subjects.
Microbiology
Mechanism of Action
Cefpodoxime is a bactericidal agent that acts by inhibition of bacterial cell wall synthesis.
Cefpodoxime has activity in the presence of some beta-lactamases, both penicillinases and cephalosporinases, of Gram-negative and Gram-positive bacteria.
Mechanism of Resistance
Resistance to cefpodoxime is primarily through hydrolysis by beta-lactamase, alteration of penicillin-binding proteins (PBPs), and decreased permeability.
Cefpodoxime has been shown to be active against most isolates of the following bacteria, both in vitro and in clinical infections as described in the Indications and Usage (1) section:
Gram-positive bacteria
Staphylococcus aureus (methicillin-susceptible strains, including those producing penicillinases)
Staphylococcus saprophyticus
Streptococcus pneumoniae (excluding penicillin-resistant isolates)
Streptococcus pyogenes
Gram-negative bacteria
Escherichia coli
Klebsiella pneumoniae
Proteus mirabilis
Haemophilus influenzae (including beta-lactamase producing isolates)
Moraxella catarrhalis
Neisseria gonorrhoeae (including penicillinase-producing isolates)
The following in vitro data are available, but their clinical significance is unknown. At least 90 percent of the following microorganisms exhibit an in vitro minimum inhibitory concentration (MIC) less than or equal to the susceptible breakpoint for cefpodoxime. However, the efficacy of cefpodoxime in treating clinical infections due to these microorganisms has not been established in adequate and well controlled clinical trials.
Gram-positive bacteria
Streptococcus agalactiae
Streptococcus spp. (Groups C, F, G)
Gram-negative bacteria
Citrobacterdiversus
Klebsiellaoxytoca
Proteus vulgaris
Providenciarettgeri
Haemophilusparainfluenzae
Anaerobic Gram-positive bacteria
Peptostreptococcusmagnus
Susceptibility Test Methods
For specific information regarding susceptibility test interpretive criteria and associated test methods and quality control standards recognized by FDA for this drug, please see: https://www.fda.gov/STIC

INDICATIONS AND USAGE

Cefpodoxime proxetil is indicated for the treatment of patients with mild to moderate infections caused by susceptible strains of the designated microorganisms in the conditions listed below.
Recommended dosages, durations of therapy, and applicable patient populations vary among these infections. Please see DOSAGE AND ADMINISTRATION for specific recommendations.
Acute otitis media caused by Streptococcus pneumoniae (excluding penicillin-resistant strains), Streptococcus pyogenes, Haemophilusinfluenzae (including beta-lactamase-producing strains), or Moraxella (Branhamella) catarrhalis (including beta-lactamase-producing strains).
Pharyngitis and/or tonsillitis caused by Streptococcus pyogenes.
NOTE: Only penicillin by the intramuscular route of administration has been shown to be effective in the prophylaxis of rheumatic fever. Cefpodoxime proxetil is generally effective in the eradication of streptococci from the oropharynx. However, data establishing the efficacy of cefpodoxime proxetil for the prophylaxis of subsequent rheumatic fever are not available.
Community-acquired pneumonia caused by S. pneumoniae or H. Influenzae (including beta-lactamase-producing strains).
Acute bacterial exacerbation of chronic bronchitis caused by S. pneumoniae, H. influenzae beta-lactamase-producing strains only), or M. catarrhalis. Data are insufficient at this time to establish efficacy in patients with acute bacterial exacerbations of chronic bronchitis caused by beta-lactamase-producing strains of H. influenzae.
Acute, uncomplicated urethral and cervical gonorrhea caused by Neisseria gonorrhoeae (including penicillinase-producing strains).
Acute, uncomplicated ano-rectal infections in women due to Neisseria gonorrhoeae (including penicillinase-producing strains).
NOTE: The efficacy of cefpodoxime in treating male patients with rectal infections caused by N. gonorrhoeae has not been established. Data do not support the use of cefpodoxime proxetil in the treatment of pharyngeal infections due to N. gonorrhoeae in men or women.
Uncomplicated skin and skin structure infections caused by Staphylococcus aureus (including penicillinase-producing strains) or Streptococcus pyogenes. Abscesses should be surgically drained as clinically indicated.
NOTE: In clinical trials, successful treatment of uncomplicated skin and skin structure infections was dose-related. The effective therapeutic dose for skin infections was higher than those used in other recommended indications. (See DOSAGE AND ADMINISTRATION.)
Acute maxillary sinusitis caused by Haemophilusinfluenzae (including beta-lactamase-producing strains), Streptococcus pneumoniae, and Moraxella catarrhalis.
Uncomplicated urinary tract infections (cystitis) caused by Escherichia coli, Klebsiellapneumoniae, Proteus mirabilis, or Staphylococcus saprophyticus.
NOTE: In considering the use of cefpodoxime proxetil in the treatment of cystitis, cefpodoxime proxetil’s lower bacterial eradication rates should be weighed against the increased eradication rates and different safety profiles of some other classes of approved agents. (See CLINICAL STUDIES section.)
Appropriate specimens for bacteriological examination should be obtained in order to isolate and identify causative organisms and to determine their susceptibility to cefpodoxime. Therapy may be instituted while awaiting the results of these studies. Once these results become available, antimicrobial therapy should be adjusted accordingly.
To reduce the development of drug-resistant bacteria and maintain the effectiveness of cefpodoxime proxetil tablets, and other antibacterial drugs, cefpodoxime proxetil tablets should be used only to treat or prevent infections that are proven or strongly suspected to be caused by susceptible bacteria. When culture and susceptibility information are available, they should be considered in selecting or modifying antibacterial therapy. In the absence of such data, local epidemiology and susceptibility patterns may contribute to the empiric selection of therapy.

CONTRAINDICATIONS

Cefpodoxime proxetil is contraindicated in patients with a known allergy to cefpodoxime or to the cephalosporin group of antibiotics.

WARNINGS

BEFORE THERAPY WITH CEFPODOXIME PROXETIL IS INSTITUTED, CAREFUL INQUIRY SHOULD BE MADE TO DETERMINE WHETHER THE PATIENT HAS HAD PREVIOUS HYPERSENSITIVITY REACTIONS TO CEFPODOXIME, OTHER CEPHALOSPORINS, PENICILLINS, OR OTHER DRUGS. IF CEFPODOXIME IS TO BE ADMINISTERED TO PENICILLIN SENSITIVE PATIENTS, CAUTION SHOULD BE EXERCISED BECAUSE CROSS HYPERSENSITIVITY AMONG BETA-LACTAM ANTIBIOTICS HAS BEEN CLEARLY DOCUMENTED AND MAY OCCUR IN UP TO 10% OF PATIENTS WITH A HISTORY OF PENICILLIN ALLERGY. IF AN ALLERGIC REACTION TO CEFPODOXIME PROXETIL OCCURS, DISCONTINUE THE DRUG.
SERIOUS ACUTE HYPERSENSITIVITY REACTIONS MAY REQUIRE TREATMENT WITH EPINEPHRINE AND OTHER EMERGENCY MEASURES, INCLUDING OXYGEN, INTRAVENOUS FLUIDS, INTRAVENOUS ANTIHISTAMINE, AND AIRWAY MANAGEMENT, AS CLINICALLY INDICATED.
Clostridium difficile associated diarrhea (CDAD) has been reported with use of nearly all antibacterial agents, including cefpodoxime proxetil tablets, and may range in severity from mild diarrhea to fatal colitis. Treatment with antibacterial agents alters the normal flora of the colon leading to overgrowth of C. difficile.
C. difficile produces toxins A and B which contribute to the development of CDAD. Hypertoxin producing strains of C. difficile cause increased morbidity and mortality, as these infections can be refractory to antimicrobial therapy and may require colectomy. CDAD must be considered in all patients who present with diarrhea following antibiotic use. Careful medical history is necessary since CDAD has been reported to occur over two months after the administration of antibacterial agents.
If CDAD is suspected or confirmed, ongoing antibiotic use not directed against C. difficile may need to be discontinued. Appropriate fluid and electrolyte management, protein supplementation, antibiotic treatment of C. difficile, and surgical evaluation should be instituted as clinically indicated.
A concerted effort to monitor for C. difficile in cefpodoxime-treated patients with diarrhea was undertaken because of an increased incidence of diarrhea associated with C. difficile in early trials in normal subjects. C. difficile organisms or toxin was reported in 10% of the cefpodoxime-treated adult patients with diarrhea; however, no specific diagnosis of pseudomembranous colitis was made in these patients.
In post-marketing experience outside the United States, reports of pseudomembranous colitis associated with the use of cefpodoxime proxetil have been received.

PRECAUTIONS

General

In patients with transient or persistent reduction in urinary output due to renal insufficiency, the total daily dose of cefpodoxime proxetil should be reduced because high and prolonged serum antibiotic concentrations can occur in such individuals following usual doses. Cefpodoxime, like other cephalosporins, should be administered with caution to patients receiving concurrent treatment with potent diuretics. (See DOSAGE AND ADMINISTRATION.)

As with other antibiotics, prolonged use of cefpodoxime proxetil may result in overgrowth of non-susceptible organisms. Repeated evaluation of the patient’s condition is essential. If superinfection occurs during therapy, appropriate measures should be taken.

Prescribing cefpodoxime proxetil tablets in the absence of a proven or strongly suspected bacterial infection or a prophylactic indication is unlikely to provide benefit to the patient and increases the risk of the development of drug-resistant bacteria.

Information for Patients

Patients should be counseled that antibacterial drugs including cefpodoxime proxetil tablets, USP should only be used to treat bacterial infections. They do not treat viral infections (e.g., the common cold). When cefpodoxime proxetil tablets, USP is prescribed to treat a bacterial infection, patients should be told that although it is common to feel better early in the course of therapy, the medication should be taken exactly as directed. Skipping doses or not completing the full course of therapy may (1) decrease the effectiveness of the immediate treatment and (2) increase the likelihood that bacteria will develop resistance and will not be treatable by cefpodoxime proxetil tablets, USP or other antibacterial drugs in the future.

Diarrhea is a common problem caused by antibiotics which usually ends when the antibiotic is discontinued. Sometimes after starting treatment with antibiotics, patients can develop watery and bloody stools (with or without stomach cramps and fever) even as late as two or more months after having taken the last dose of the antibiotic. If this occurs, patients should contact their physician as soon as possible.

Drug Interactions

Antacids
Concomitant administration of high doses of antacids (sodium bicarbonate and aluminum hydroxide) or H2 blockers reduces peak plasma levels by 24% to 42% and the extent of absorption by 27% to 32%, respectively. The rate of absorption is not altered by these concomitant medications. Oral anti-cholinergics (e.g., propantheline) delay peak plasma levels (47% increase in Tmax), but do not affect the extent of absorption (AUC).
Probenecid
As with other beta-lactam antibiotics, renal excretion of cefpodoxime was inhibited by probenecid and resulted in an approximately 31% increase in AUC and 20% increase in peak cefpodoxime plasma levels.
Nephrotoxic drugs
Although nephrotoxicity has not been noted when cefpodoxime proxetil was given alone, close monitoring of renal function is advised when cefpodoxime proxetil is administered concomitantly with compounds of known nephrotoxic potential.

Drug/Laboratory Test Interactions

Cephalosporins, including cefpodoxime proxetil, are known to occasionally induce a positive direct Coombs’ test.

Carcinogenesis, Mutagenesis, Impairment of Fertility

Long-term animal carcinogenesis studies of cefpodoxime proxetil have not been performed.

Mutagenesis studies of cefpodoxime, including the Ames test both with and without metabolic activation, the chromosome aberration test, the unscheduled DNA synthesis assay, mitotic recombination and gene conversion, the forward gene mutation assay and the in vivo micronucleus test, were all negative. No untoward effects on fertility or reproduction were noted when 100 mg/kg/day or less (2 times the human dose based on mg/m2) was administered orally to rats.

Pregnancy

Teratogenic Effects
Pregnancy Category B

Cefpodoxime proxetil was neither teratogenic nor embryocidal when administered to rats during organogenesis at doses up to 100 mg/kg/day (2 times the human dose based on mg/m2) or to rabbits at doses up to 30 mg/kg/day (1 to 2 times the human dose based on mg/m2).
There are, however, no adequate and well-controlled studies of cefpodoxime proxetil use in pregnant women. Because animal reproduction studies are not always predictive of human response, this drug should be used during pregnancy only if clearly needed.

Labor and Delivery

Cefpodoxime proxetil has not been studied for use during labor and delivery. Treatment should only be given if clearly needed.

Nursing Mothers

Cefpodoxime is excreted in human milk. In a study of 3 lactating women, levels of cefpodoxime in human milk were 0%, 2% and 6% of concomitant serum levels at 4 hours following a 200 mg oral dose of cefpodoxime proxetil. At 6 hours post-dosing, levels were 0%, 9% and 16% of concomitant serum levels. Because of the potential for serious reactions in nursing infants, a decision should be made whether to discontinue nursing or to discontinue the drug, taking into account the importance of the drug to the mother.

Pediatric Use

Safety and efficacy in infants less than 2 months of age have not been established.

Geriatric Use

Of the 3338 patients in multiple-dose clinical studies of cefpodoxime proxetil film-coated tablets, 521 (16%) were 65 and over, while 214 (6%) were 75 and over. No overall differences in effectiveness or safety were observed between the elderly and younger patients. In healthy geriatric subjects with normal renal function, cefpodoxime half-life in plasma averaged 4.2 hours and urinary recovery averaged 21% after a 400 mg dose was given every 12 hours for 15 days. Other pharmacokinetic parameters were unchanged relative to those observed in healthy younger subjects.

Dose adjustment in elderly patients with normal renal function is not necessary.

ADVERSE REACTIONS

Clinical Trials
Film-coated Tablets (Multiple dose)
In clinical trials using multiple doses of cefpodoxime proxetil film-coated tablets, 4696 patients were treated with the recommended dosages of cefpodoxime (100 to 400 mg Q 12 hours). There were no deaths or permanent disabilities thought related to drug toxicity. One-hundred twenty-nine (2.7%) patients discontinued medication due to adverse events thought possibly or probably related to drug toxicity. Ninety-three (52%) of the 178 patients who discontinued therapy (whether thought related to drug therapy or not) did so because of gastrointestinal disturbances, nausea, vomiting, or diarrhea. The percentage of cefpodoxime proxetil-treated patients who discontinued study drug because of adverse events was significantly greater at a dose of 800 mg daily than at a dose of 400 mg daily or at a dose of 200 mg daily. Adverse events thought possibly or probably related to cefpodoxime in multiple-dose clinical trials (N=4696 cefpodoxime-treated patients) were:
Incidence Greater Than 1 %

Diarrhea | 7 %

Diarrhea or loose stools were dose-related: decreasing from 10.4% of patients receiving 800 mg per day to 5.7% for those receiving 200 mg per day. Of patients with diarrhea, 10% had C. difficile organism or toxin in the stool.(See WARNINGS.)

Nausea | 3.3 %
Vaginal Fungal Infections | 1 %
Vulvovaginal Infections | 1.3 %
Abdominal Pain | 1.2 %
Headache | 1 %

Incidence Less Than 1 %: By body system in decreasing order
Clinical Studies
Adverse events thought possibly or probably related to cefpodoxime proxetil that occurred in less than 1% of patients (N=4696)
Body – fungal infections, abdominal distention, malaise, fatigue, asthenia, fever, chest pain, back pain, chills, generalized pain, abnormal microbiological tests, moniliasis, abscess, allergic reaction, facial edema, bacterial infections, parasitic infections, localized edema, localized pain.
Cardiovascular – congestive heart failure, migraine, palpitations, vasodilation, hematoma, hypertension, hypotension.
Digestive – vomiting, dyspepsia, dry mouth, flatulence, decreased appetite, constipation, oral moniliasis, anorexia, eructation, gastritis, mouth ulcers, gastrointestinal disorders, rectal disorders, tongue disorders, tooth disorders, increased thirst, oral lesions, tenesmus, dry throat, toothache.
Hemic and Lymphatic – anemia.
Metabolic and Nutritional – dehydration, gout, peripheral edema, weight increase.
Musculo-skeletal – myalgia.
Nervous – dizziness, insomnia, somnolence, anxiety, shakiness, nervousness, cerebral infarction, change in dreams, impaired concentration, confusion, nightmares, paresthesia, vertigo.
Respiratory – asthma, cough, epistaxis, rhinitis, wheezing, bronchitis, dyspnea, pleural effusion, pneumonia, sinusitis.
Skin – urticaria, rash, pruritus non-application site, diaphoresis, maculopapular rash, fungal dermatitis, desquamation, dry skin non-application site, hair loss, vesiculobullous rash, sunburn.
Special Senses – taste alterations, eye irritation, taste loss, tinnitus.
Urogenital – hematuria, urinary tract infections, metrorrhagia, dysuria, urinary frequency, nocturia, penile infection, proteinuria, vaginal pain.
Film-coated Tablets (Single dose)
In clinical trials using a single dose of cefpodoxime proxetil film-coated tablets, 509 patients were treated with the recommended dosage of cefpodoxime (200 mg). There were no deaths or permanent disabilities thought related to drug toxicity in these studies.
Adverse events thought possibly or probably related to cefpodoxime in single-dose clinical trials conducted in the United States were:
Incidence Greater Than 1%

Nausea | 1.4 %
Diarrhea | 1.2 %

Incidence Less Than 1 %
Central Nervous System: Dizziness, headache, syncope.
Dermatologic: Rash.
Genital: Vaginitis.
Gastrointestinal: Abdominal pain.
Psychiatric: Anxiety.
Laboratory Changes
Significant laboratory changes that have been reported in adult and pediatric patients in clinical trials of cefpodoxime proxetil, without regard to drug relationship, were:
Hepatic: Transient increases in AST (SGOT), ALT (SGPT), GGT, alkaline phosphatase, bilirubin, and LDH.
Hematologic: Eosinophilia, leukocytosis, lymphocytosis, granulocytosis, basophilia, monocytosis, thrombocytosis, decreased hemoglobin, decreased hematocrit, leukopenia, neutropenia, lymphocytopenia, thrombocytopenia, thrombocythemia, positive Coombs’ test, and prolonged PT, and PTT.
Serum Chemistry: Hyperglycemia, hypoglycemia, hypoalbuminemia, hypoproteinemia, hyperkalemia, and hyponatremia.
Renal: Increases in BUN and creatinine.
Most of these abnormalities were transient and not clinically significant.
Post-marketing Experience
The following serious adverse experiences have been reported: allergic reactions including Stevens-Johnson syndrome, toxic epidermal necrolysis, erythema multiforme and serum sickness-like reactions, pseudomembranous colitis, bloody diarrhea with abdominal pain, ulcerative colitis, rectorrhagia with hypotension, anaphylactic shock, acute liver injury, in utero exposure with miscarriage, purpuric nephritis, pulmonary infiltrate with eosinophilia, and eyelid dermatitis.
One death was attributed to pseudomembranous colitis and disseminated intravascular coagulation.
Cephalosporin Class Labeling
In addition to the adverse reactions listed above which have been observed in patients treated with cefpodoxime proxetil, the following adverse reactions and altered laboratory tests have been reported for cephalosporin class antibiotics:
Adverse Reactions and Abnormal Laboratory Tests: Renal dysfunction, toxic nephropathy, hepatic dysfunction including cholestasis, aplastic anemia, hemolytic anemia, serum sickness-like reaction, hemorrhage, agranulocytosis, and pancytopenia.
Several cephalosporins have been implicated in triggering seizures, particularly in patients with renal impairment when the dosage was not reduced.(See DOSAGE AND ADMINISTRATION and OVERDOSAGE.) If seizures associated with drug therapy occur, the drug should be discontinued.
Anticonvulsant therapy can be given if clinically indicated.

OVERDOSAGE

In acute rodent toxicity studies, a single 5 g/kg oral dose produced no adverse effects.
In the event of serious toxic reaction from overdosage, hemodialysis or peritoneal dialysis may aid in the removal of cefpodoxime from the body, particularly if renal function is compromised.
The toxic symptoms following an overdose of beta-lactam antibiotics may include nausea, vomiting, epigastric distress, and diarrhea.

DOSAGE AND ADMINISTRATION

(See INDICATIONS AND USAGE for indicated pathogens.)
Film-coated Tablets
Cefpodoxime Proxetil Tablets, USP should be administered orally with food to enhance absorption. (See CLINICAL PHARMACOLOGY.)
The recommended dosages, durations of treatment, and applicable patient population are as described in the following chart:

Adults and Adolescents (age 12 years and older)

Type of Infection | Total Daily Dose | Dose Frequency | Duration
Pharyngitis and/or tonsillitis | 200 mg | 100 mg Q 12 hours | 5 to 10 days
Acute community acquired - pneumonia | 400 mg | 200 mg Q 12 hours | 14 days
Acute bacterial exacerbations of chronic bronchitis | 400 mg | 200 mg Q 12 hours | 10 days
Uncomplicated gonorrhea (men and women) and rectal gonococcal infections (women) | 200 mg | single dose
Skin and skin structure | 800 mg | 400 mg Q 12 hours | 7 to 14 days
Acute maxillary sinusitis | 400 mg | 200 mg Q 12 hours | 10 days
Uncomplicated urinary tract infection | 200 mg | 100 mg Q 12 hours | 7 days

Patients with Renal Dysfunction
For patients with severe renal impairment (<30 mL/min creatinine clearance), the dosing intervals should be increased to Q 24 hours. In patients maintained on hemodialysis, the dose frequency should be 3 times/week after hemodialysis.
When only the serum creatinine level is available, the following formula (based on sex, weight, and age of the patient) may be used to estimate creatinine clearance (mL/min). For this estimate to be valid, the serum creatinine level should represent a steady state of renal function.

Males: Weight (kg) × (140 - age)

(mL/min) 72 × serum creatinine (mg/100 mL)

Females: 0.85 × above value

(mL/min)

Patients with Cirrhosis
Cefpodoxime pharmacokinetics in cirrhotic patients (with or without ascites) are similar to those in healthy subjects. Dose adjustment is not necessary in this population.

HOW SUPPLIED

Cefpodoxime Proxetil Tablets, USP are available in the following strengths (cefpodoxime equivalent), colors, and sizes:
100 mg, (Orange colored, oval shaped, film coated tablets debossed with "A55" on one side and plain on other side)
Bottles of 20 NDC 51407-083-20
200 mg, (Orange colored, capsule shaped, film coated tablets debossed with "A57" on one side and plain on other side)
Bottles of 20 NDC 51407-084-20
Store at 20° to 25°C (68° to 77°F) [see USP Controlled Room Temperature].
Replace cap securely after each opening.

CLINICAL TRIALS

Cystitis
In two double-blind, 2:1 randomized, comparative trials performed in adults in the United States, cefpodoxime proxetil was compared to other beta-lactam antibiotics. In these studies, the following bacterial eradication rates were obtained at 5 to 9 days after therapy:

Pathogen | Cefpodoxime | Comparator
E. coli | 200/243 (82%) | 99/123 (80%)
Other pathogens K. pneumoniae P. mirabilis S. saprophyticus | 34/42 (81%) | 23/28 (82%)
TOTAL | 234/285 (82%) | 122/151 (81%)

In these studies, clinical cure rates and bacterial eradication rates for cefpodoxime proxetil were comparable to the comparator agents; however, the clinical cure rates and bacteriologic eradication rates were lower than those observed with some other classes of approved agents for cystitis.

Acute Otitis Media Studies
In controlled studies of acute otitis media performed in the United States, where significant rates of beta-lactamase-producing organisms were found, cefpodoxime proxetil was compared to cefixime. In these studies, using very strict evaluability criteria and microbiologic and clinical response criteria at the 4 to 21 day post-therapy follow-up, the following presumptive bacterial eradication/clinical success outcomes (cured and improved) were obtained.

Pathogen | Cefpodoxime Proxetil 5 mg/kg Q 12 h x 5 d | Cefixime
S. pneumoniae | 88/122 (72%) | 72/124 (58%)
H. influenzae | 50/76 (66%) | 61/81 (75%)
M. catarrhalis | 22/39 (56%) | 23/41 (56%)
S. pyogenes | 20/25 (80%) | 13/23 (57%)
Clinical success rate | 171/254 (67%) | 165/258 (64%)

Manufactured by:
Alkem Laboratories Ltd.,

INDIA.
Distributed by:
Ascend Laboratories, LLC
Parsippany, NJ 07054
Revised: October, 2022

PT3652

Marketed by:

GSMS, Inc.

Camarillo, CA 93012 USA

PACKAGE LABEL.PRINCIPAL DISPLAY PANEL

NDC 51407-083-20
Cefpodoxime Proxetil
Tablets, USP 100 mg*
Rx only
20 Tablets

NDC 51407-084-20
Cefpodoxime Proxetil
Tablets, USP 200 mg*
Rx only
20 Tablets